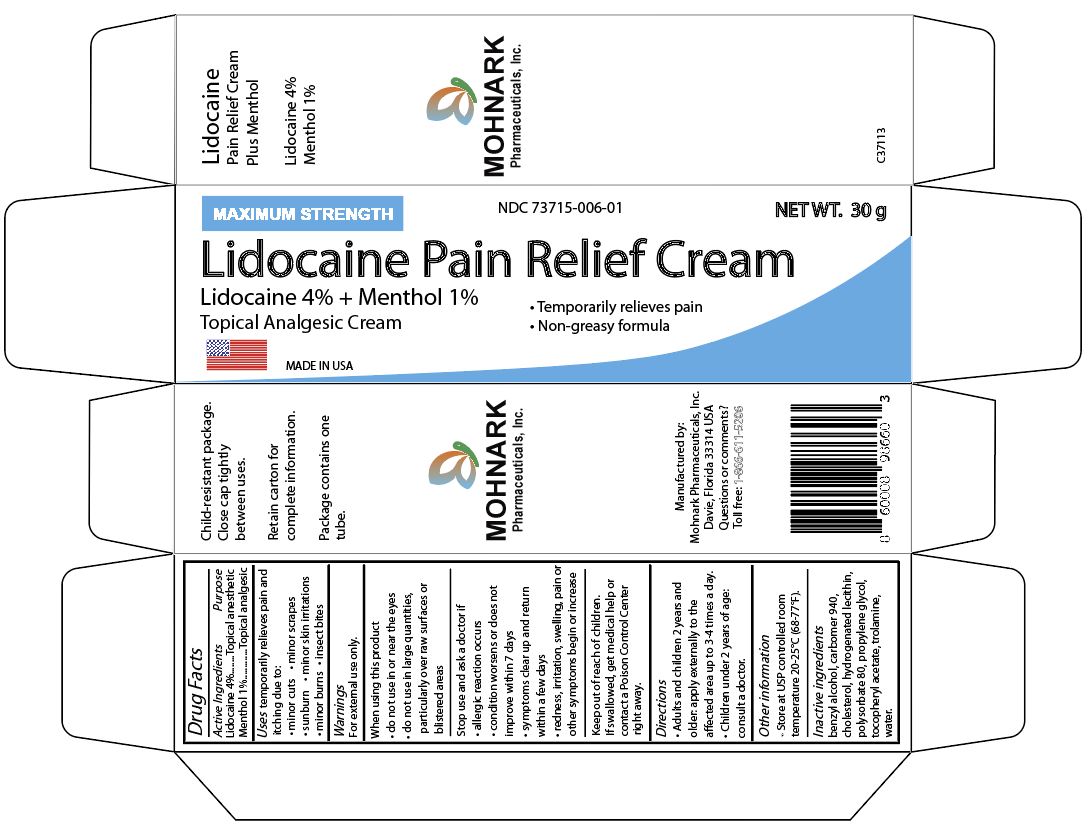 DRUG LABEL: Lidocaine 4% plus Menthol 1% Topical Anesthetic Pain Cream
NDC: 73715-006 | Form: CREAM
Manufacturer: MOHNARK PHARMACEUTICALS INC
Category: otc | Type: HUMAN OTC DRUG LABEL
Date: 20250815

ACTIVE INGREDIENTS: LIDOCAINE 4.27 g/100 g; MENTHOL 1 g/100 g
INACTIVE INGREDIENTS: POLYSORBATE 80 1 g/100 g

Lidocaine 4% Plus Menthol 1% Pain Relief Cream

Active Ingredients

Lidocaine 4%
Menthol 1%

Uses

temporarily relieves pain and itching due to:

- minor cuts
- minor scrapes
- sunburn
- minor skin irritations
- minor burns
- insect bites

Warnings

For external use only.

When using this product

• do not use in or near the eyes
• do not use in large quantities, particularly over raw surfaces or
blistered area

Stop use and ask a doctor if

• allergic reaction occurs
• condition worsens or does not
improve within 7 days
• symptoms clear up and return
within a few days
• redness, irritation, swelling, pain or
other symptoms begin or increase

Keep out of reach of children.

If swallowed, get medical help or
contact a Poison Control Center
right away.

Directions

• Adults and children 2 years and
older: apply externally to the
affected area up to 3-4 times a day.
• Children under 2 years of age:
consult a doctor.

Other information

• Store at USP controlled room
temperature 20-25°C (68-77°F).

Inactive Ingredients

benzyl alcohol, carbomer 940, cholesterol, hydrogenated lecithin,
polysorbate 80, propylene glycol, tocopheryl acetate, trolamine,
water.

Usage

Lidocaine 4% cream is indicated for use on normal intact skin for temporary relief of pain and itching due to minor cuts, minor scrapes, minor skin irritations, minor burns and insect bites.
Lidocaine 4% cream is not recommended for internal use, in the or near the eyes and in large quantities, particularly over raw surfaces or blistered areas.

Dosage and Administration

Adults and children 2 years and older. Apply externally to the affected area up to 3 to 4 times a day.
Children under 2 years of age. Consult a doctor.